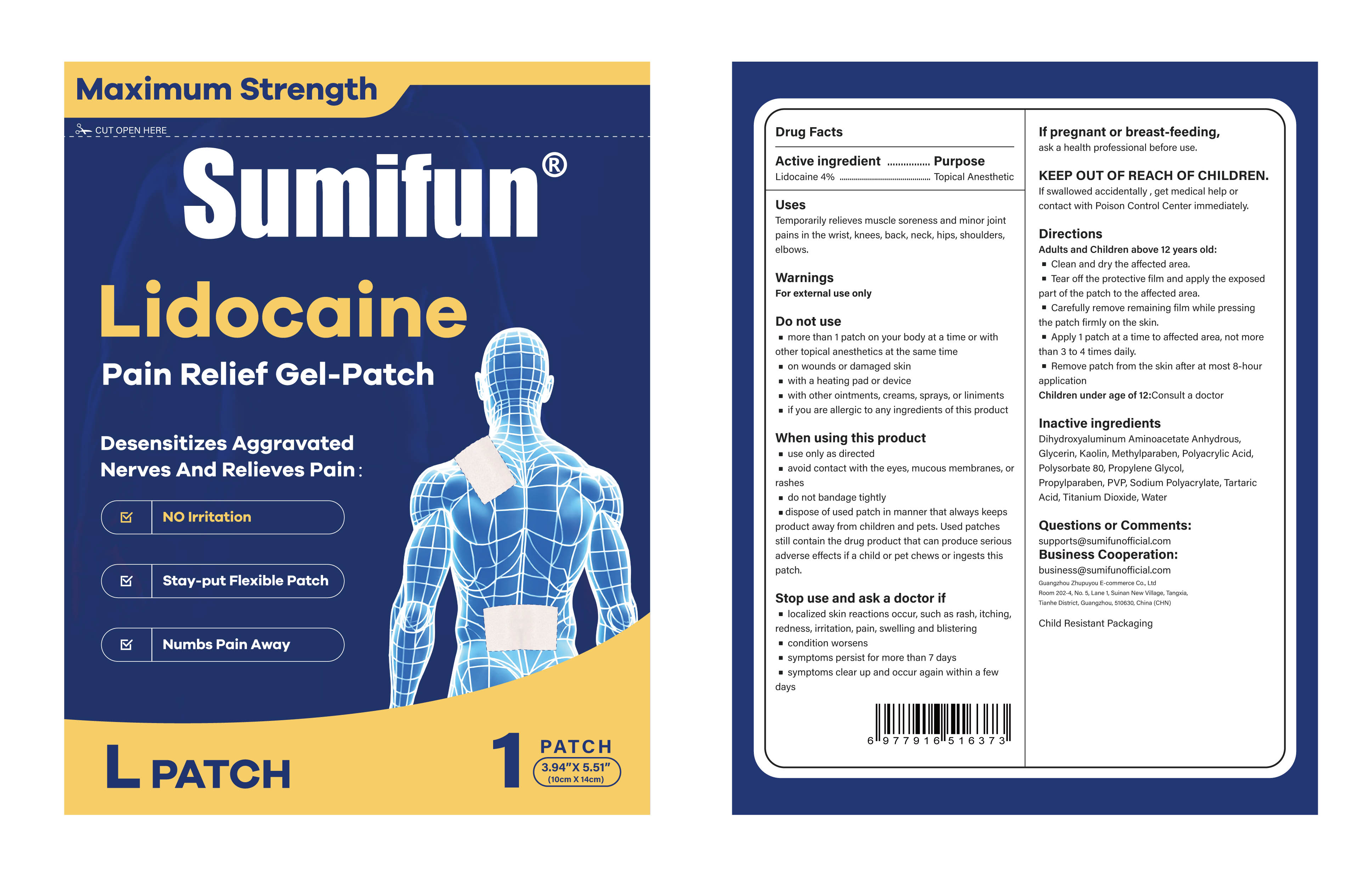 DRUG LABEL: Lidocaine Pain Relief Gel-Patch
NDC: 84165-005 | Form: PATCH
Manufacturer: Guangzhou Zhupuyou E-commerce Co., Ltd
Category: otc | Type: HUMAN OTC DRUG LABEL
Date: 20250429

ACTIVE INGREDIENTS: LIDOCAINE 0.04 g/1 g
INACTIVE INGREDIENTS: METHYLPARABEN; WATER; TITANIUM DIOXIDE; GLYCERIN; KAOLIN; TARTARIC ACID; DIHYDROXYALUMINUM AMINOACETATE ANHYDROUS; PROPYLENE GLYCOL; POVIDONE K90; SODIUM POLYACRYLATE (2500000 MW); POLYSORBATE 80; PROPYLPARABEN; POLYACRYLIC ACID (250000 MW)

Lidocaine Pain Relief Gel-Patch

ACTIVE INGREDIENT

Lidocaine 4%

PURPOSE

Topical Anesthetic

INDICATIONS AND USAGE

Temporarily relieves muscle soreness and minor jointpains in the wrist, knces, back, neck, hips, shouldcrs,elbows.

WARNINGS

For external use only

DO NOT USE

· more than 1 patch on your body at a time or with other topical anesthetics at the same time

· on wounds or damaged skin

· with a heating pad or device

· with other ointments, creams, sprays, or liniments

· if you are allergic to any ingredients of this product

WHEN USING

· use only as directed

· avoid contact with the eyes, mucous membranes, or rashes

· do not bandage tightly

· dispose of used patch in manner that always keeps product away from children and pets. Used patches still contain the drug product that can produce serious adverse effects if a child or pet chews or ingests this patch.

STOP USE

· localized skin reactions occur, such as rash, itching, redness, irritation, pain, swelling and blistering

· condition worsens

· symptoms persist for more than 7 days

· symptoms clear up and occur again within a few days

KEEP OUT OF REACH OF CHILDREN

ask a health professional before use.

DOSAGE AND ADMINISTRATION

Adults and Children above 12 years old:

· Clean and dry the affected area.

· Tear off the protective film and apply the exposed part of the patch to the affected area.

· Carefully remove remaining film while pressing the patch firmly on the skin.

· Apply 1 patch at a time to affected area, not more than 3 to 4 times daily.

· Remove patch from the skin after at most 8-hour application

Children under age of 12:Consult a doctor

INACTIVE INGREDIENT

Dihydroxyaluminum Aminoacetate Anhydrous
Glycerin
Kaolin
Methylparaben
Polyacrylic Acid
Polysorbate 80
Propylene Glycol
Propylparaben
PVP
Sodium Polyacrylate
Tartaric Acid
Titanium Dioxide
Water